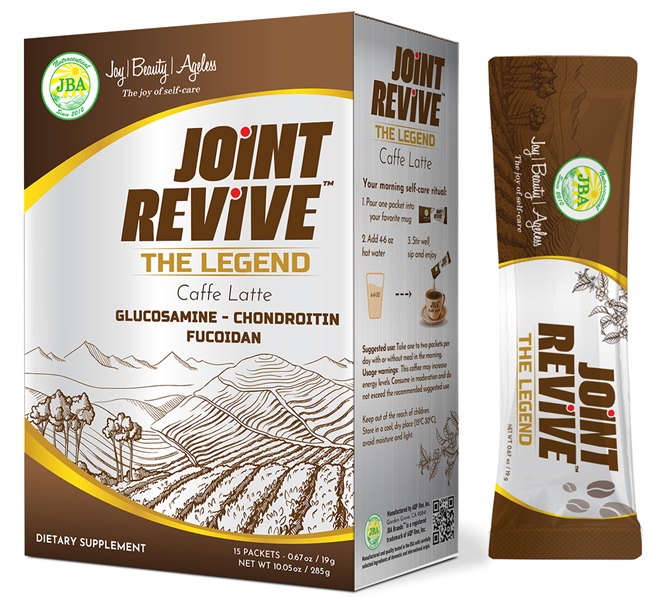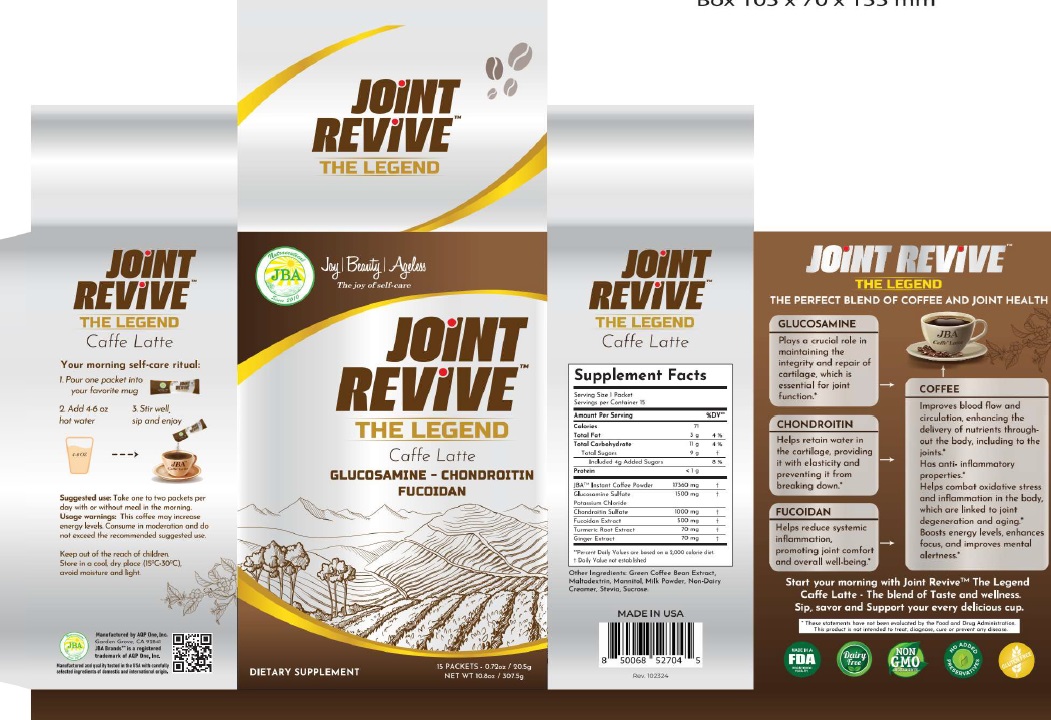 DRUG LABEL: JBA Joint Revive TM The Legend Caffe Latte
NDC: 13411-858 | Form: POWDER
Manufacturer: Advanced Pharmaceutical Services, Inc. Dba Affordable Quality Pharmaceuticals
Category: otc | Type: HUMAN OTC DRUG LABEL
Date: 20251128

ACTIVE INGREDIENTS: LAMINARIA JAPONICA 500 mg/1 1; CHONDROITIN SULFATE (BOVINE) 1000 mg/1 1; GLUCOSAMINE SULFATE POTASSIUM CHLORIDE 1500 mg/1 1
INACTIVE INGREDIENTS: COFFEE BEAN; MALTODEXTRIN; MANNITOL; SKIM MILK; STEVIOSIDE; SUCROSE

Identity

Dietary supplement

Direction

Take one or two packets per day with or without meal in the morning.

Safe handling warning

JOINT REVIVE™ THE LEGEND CAFFE LATTE
Glucosamine – Chondroitin - Fucoidan

The Perfect Blend of Coffee and Joint Health
Glucosamine
Plays a crucial role in maintaining the integrity and repair of cartilage, which is essential for joint function*

Chondroitin
Helps retain water in the cartilage, providing it with elasticity and preventing from breaking down.*

Fucoidan
Helps reduce systemic inflammation, promoting joint comfort and overall well-being.*

Coffee
Improves blood flow and circulation. Enhance the delivery of nutrients through-out the body including the joints.*
Has anti-inflammatory properties.*
Helps combat oxidative stress and inflammation in the body, which are linked to joint degeneration and aging.*
Boosts energy levels, enhances focus, and improves mental alertness.*

Start your morning with Joint ReviveTM The Legend Caffe Latte. The blend of taste and wellness. Sip, savor and support your every delicious cup.

* These statements have not been evaluated by the Food & Drug Administration. This product is not intended to diagnose, treat, cure, or prevent any disease.

PRECAUTIONS

This coffee may increase energy levels. Consume in moderation and do not exceed the recommended suggested use.

Keep Out of The Reach of Children. Store in a cool, dry place (59°F-86°F), avoid moisture and light.

WARNINGS

Other Ingredients

Green Coffee Bean Extract, Maltodextrin, Mannitol, Milk Powder, Stevia, Sucrose